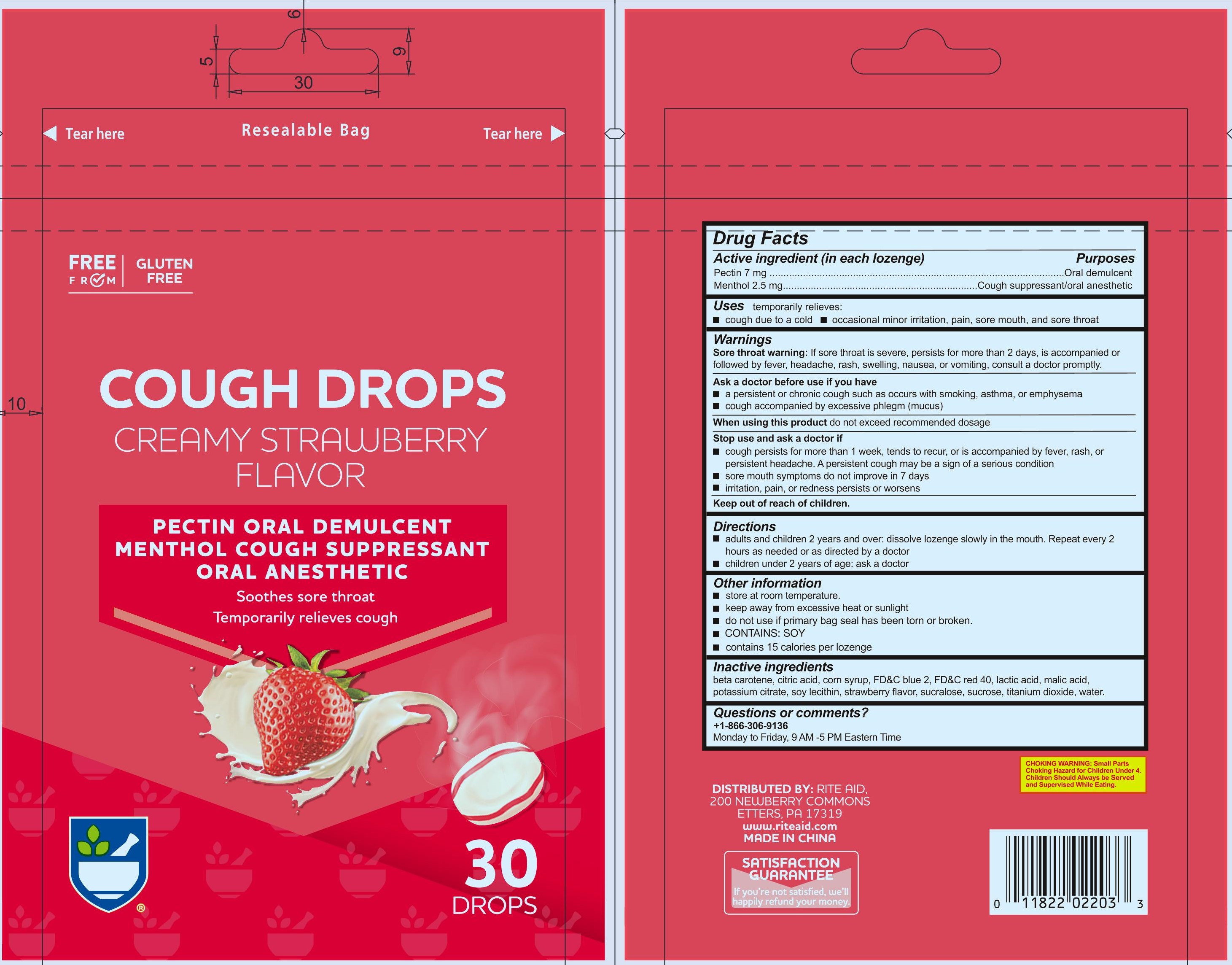 DRUG LABEL: Creamy Strawberry Flavor Cough Drop
NDC: 83698-221 | Form: LOZENGE
Manufacturer: Xiamen Kang Zhongyuan Biotechnology Co., Ltd.
Category: otc | Type: HUMAN OTC DRUG LABEL
Date: 20251226

ACTIVE INGREDIENTS: MENTHOL 2.5 mg/1 1; PECTIN 7 mg/1 1
INACTIVE INGREDIENTS: BETA CAROTENE; CITRIC ACID MONOHYDRATE; FD&C BLUE NO. 2; CORN SYRUP; LECITHIN, SOYBEAN; SUCRALOSE; SUCROSE; WATER; FD&C RED NO. 40; LACTIC ACID; MALIC ACID; POTASSIUM CITRATE; TITANIUM DIOXIDE

RA Creamy Strawberry Cough Drop, Menthol 2.5 mg, Pectin 7 mg

Active ingredeint (in each Lozenge)

Pectin 7 mg

Menthol 2.5 mg

Purpose

Oral demulcent

Cough suppressant/Oral anesthetic

Uses

temporarily relieves:

- cough due to a cold
- occasional minor irritation, pain, sore mouth, and sore throat

Warnings

Sore throat warning:If sore throat is severe, persists for more than 2 days, is accompanied or followed by fever, headache, rash, swelling, nausea, or vomiting, consult a doctor promptly.

Ask a doctor before use if you have

- persistent or chronic cough such as occurs with smoking, asthma, or emphysema
- cough accompanied by excessive phlegm (mucus)

When using this product do not exceed recommended dosage

Stop use and ask doctor if

- cough persists for more than 1 week, tends to recur, or is accompanied by fever, rash, or persistent headache. A persistent cough may be a sign of a serious condition.
- sore mouth does not improve in 7 days
- irritation, pain or redness persists or worsens

Keep out of reach of children.

Directions

- adults and children 2 years and over: dissolve lozenge slowly in mouth. Repeat every 2 hours as needed or as directed by a doctor.
- children under 2 years: ask a doctor

Other information

- Store at room termperature
- keep away from excessive heat or sunlight
- do not use if primary bag seal has been torn or broken
- CONTAINS: SOY
- contains 15 calories per drop

Inactive ingredients

Beta carotene, citric acid, corn syrup, FD&C blue 2, FD&C red 40, lactic acid, malic acid, potassium citrate, soy lecithin, strawberry flavor, sucralose, sucrose, titanium dioxide, water

Questions or comments?

+1-866-306-9136

Monday to Friday, 9AM - 5PM Eastern Time

PACKAGE LABEL

Add image transcription here...